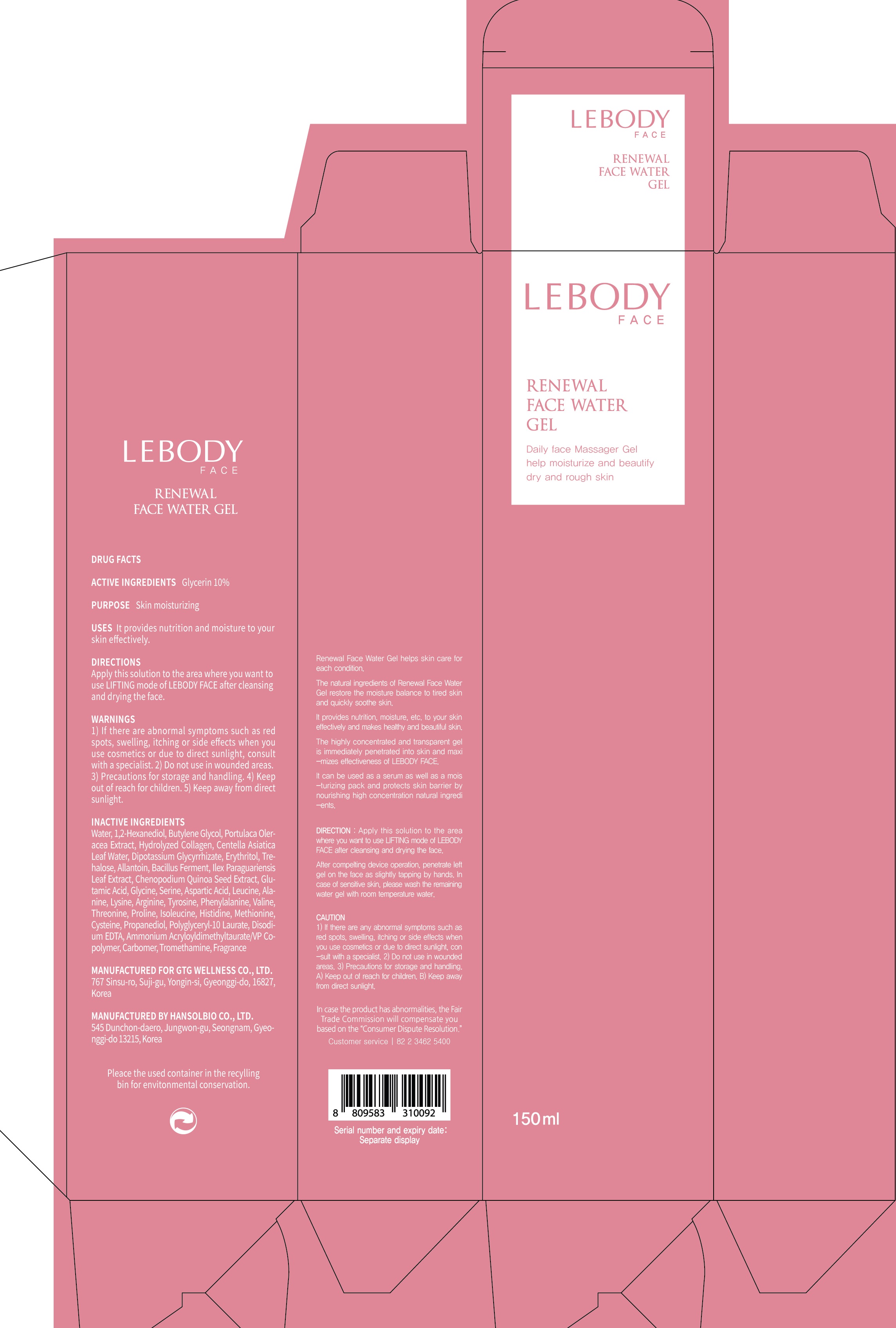 DRUG LABEL: LEBODY FACE RENEWAL
NDC: 71080-0004 | Form: GEL
Manufacturer: GTG Wellness Co., Ltd.
Category: otc | Type: HUMAN OTC DRUG LABEL
Date: 20171226

ACTIVE INGREDIENTS: Glycerin 15.0 g/150 mL
INACTIVE INGREDIENTS: Water; 1,2-Hexanediol

ACTIVE INGREDIENT

Active ingredients: Glycerin 10%

INACTIVE INGREDIENT

Inactive ingredients:

Water, 1,2-Hexanediol, Butylene Glycol, Portulaca Oleracea Extract, Hydrolyzed Collagen, Centella Asiatica Leaf Water, Dipotassium Glycyrrhizate, Erythritol, Trehalose, Allantoin, Bacillus Ferment, Ilex Paraguariensis Leaf Extract, Chenopodium Quinoa Seed Extract, Glutamic Acid, Glycine, Serine, Aspartic Acid, Leucine, Alanine, Lysine, Arginine, Tyrosine, Phenylalanine, Valine, Threonine, Proline, Isoleucine, Histidine, Methionine, Cysteine, Propanediol, Polyglyceryl-10 Laurate, Disodium EDTA, Ammonium Acryloyldimethyltaurate/VP Copolymer, Carbomer, Tromethamine, Fragrance

PURPOSE

Purpose: Skin moisturizing

WARNINGS

Warnings: 1) If there are abnormal symptoms such as red spots, swelling, itching or side effects when you use cosmetics or due to direct sunlight, consult with a specialist. 2) Do not use in wounded areas. 3) Precautions for storage and handling. 4) Keep out of reach for children. 5) Keep away from direct sunlight.

KEEP OUT OF REACH OF CHILDREN

Keep out of reach for children.

Uses

Uses: It provides nutrition and moisture to your skin effectively.

Directions

Directions: Apply this solution to the area where you want to use LIFTING mode of LEBODY FACE after cleansing and drying the face.